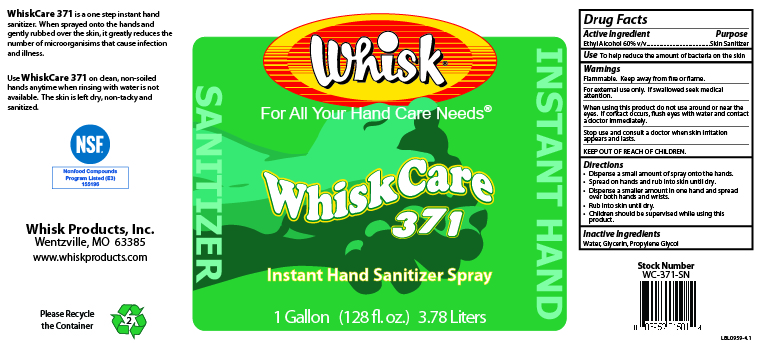 DRUG LABEL: WhiskCare 371
NDC: 65585-372 | Form: SPRAY
Manufacturer: Whisk Products, Inc.
Category: otc | Type: HUMAN OTC DRUG LABEL
Date: 20240703

ACTIVE INGREDIENTS: ALCOHOL 600 mL/1 L
INACTIVE INGREDIENTS: GLYCERIN; PROPYLENE GLYCOL; WATER

WhiskCare 371

Active Ingredient

Ethyl Alcohol 60% v/v

Purpose

Skin Sanitizer

Use

To help reduce the amount of bacteria on the skin

Warnings

Flammable. Keep away from fire or flame.

For external use only. If swallowed seek medical attention.

When using this product do not use around or near the eyes. If contact occurs, flush eyes with water and contact a doctor immediately.

Stop use and consult a doctor when skin irritation appears and lasts.

KEEP OUT OF REACH OF CHILDREN.

Directions

- Dispense a small amount of spray onto the hands.
- Spread on hands and rub into skin until dry.
- Dispense a smaller amount in one hand and spread over both hands and wrists.
- Rub into skin until dry.
- Children should be supervised while using this product.

Inactive Ingredients

Water, Glycerin, Propylene Glycol